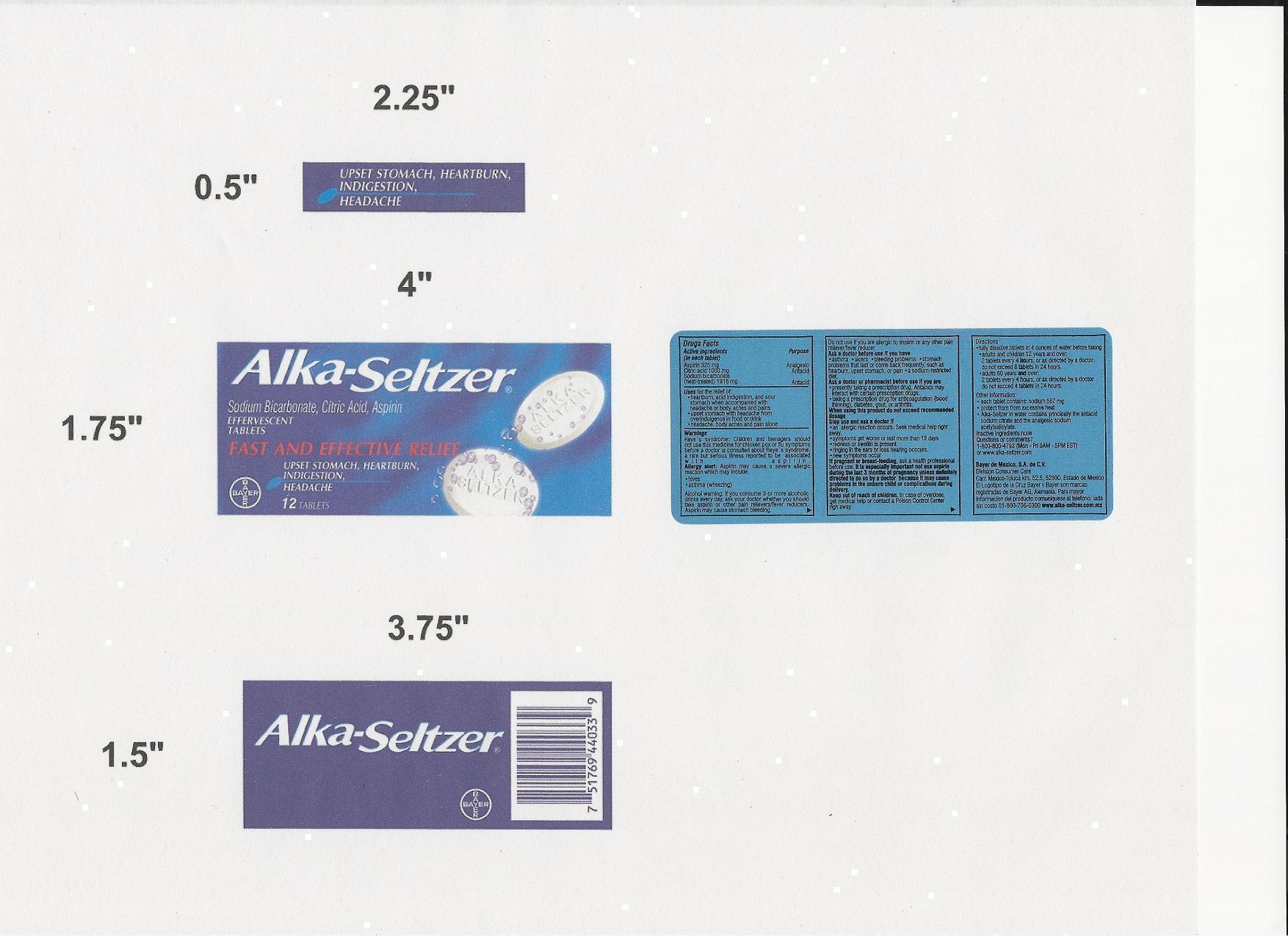 DRUG LABEL: Alka Seltzer
NDC: 53666-403 | Form: TABLET, EFFERVESCENT
Manufacturer: Salimex, S.A.
Category: otc | Type: HUMAN OTC DRUG LABEL
Date: 20121109

ACTIVE INGREDIENTS: ASPIRIN 325 mg/1 1; ANHYDROUS CITRIC ACID 1000 mg/1 1; SODIUM BICARBONATE 1916 mg/1 1

Alka Seltzer

Active Ingredients (in each tablet)

Aspirin 325 mg

Citric acid 1000 mg

Sodium Bicarbonate (heat treated) 1916 mg

Purpose

Analgesic, Antacid

Keep out of reach of children

In case of overdose, get medical help or contact a Poison Control Center right away.

Uses for the relief of:

- heartburn, acid indigestion, and sour stomach when accompanied with headache or body aches and pains
- upset stomach with headache from overindulgence in food or drink
- headache, body aches, and pain alone

Warnings

Reye's syndrome: Children and teenagers should not use this medicine for chicken pox or flu symptoms before a doctor is consulted about Reye's syndrome, a rare but serious illness reported to be associated with aspirin.

Allergy alert: Aspirin may cause a severe allergic reaction which may include:

- hives
- asthma (wheezing)

Alcohol warning: If you consume 3 or more alcoholic drinks every day, ask your doctor whether you should take aspirin or other pain relievers/fever reducers. Aspirin may cause stomach bleeding.

Directions

- fully dissolve 2 tablets in 4 ounces of water before taking
- adults and children 12 years and over: 2 tablets every 4 hours, or as directed by a doctor do not exceed 8 tablets in 24 hours
- adults 60 years and over 2 tablets every 4 hours, or as directed by a doctor do not exceed 4 tablets in 24 hours
- children under 12 years consult a doctor

Other information

- each tablet contains: sodium 567 mg
- store at room temperature. Avoid excessive heat.
- Alka-Seltzer in water contains principally the antacid sodium citrate and the analgesic sodium acetylsalicylate

Inactive ingredients

None

Questions or comments?

1-800-986-0369 (Mon – Fri 9AM – 5PM EST)
or www.alkaseltzer.com